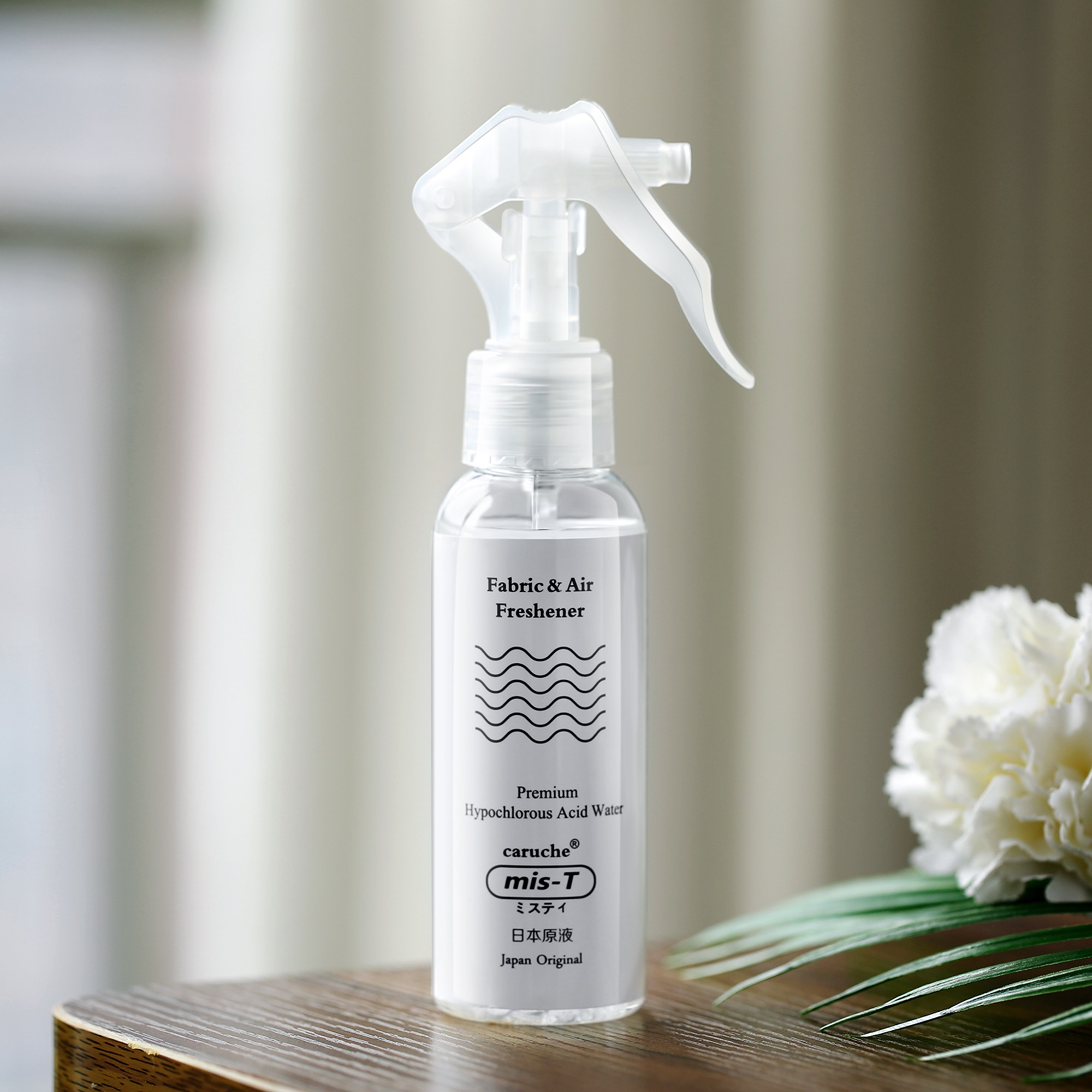 DRUG LABEL: Caruche Premium Hypochlorous Acid Water
NDC: 74841-001 | Form: LIQUID
Manufacturer: NAP Industrial (Shenzhen) Limited
Category: otc | Type: HUMAN OTC DRUG LABEL
Date: 20200426

ACTIVE INGREDIENTS: HYPOCHLOROUS ACID 0.4 mg/1 mL
INACTIVE INGREDIENTS: WATER

Caruche Premium Hypochlorous Acid Water

HYPOCHLOROUS ACID 0,4mg/ml

Water

ACTIVE INGREDIENT

HYPOCHLOROUS ACID 0.4mg/ml

PURPOSE

Products used to kill bacteria and viruses, prevent disease, and suppress spread

INDICATIONS AND USAGE

Sterilize by spraying on objects or skin surface

WARNINGS

For external use only.

DO NOT USE

in children less than 2 months of age
on open skin wounds

When using this product keep out of eyes, ears, and mouth. In case of contact with eyes, rinse eyes thoroughly with water.
Stop use and ask a doctor if irritation or rash occurs. These may be signs of a serious condition.
Keep out of reach of children. If swallowed, get medical help or contact a Poison Control Center right away.

Stop use and ask a doctor if irritation or rash occurs. These may be signs of a serious condition.

Keep out of reach of children. If swallowed, get medical help or contact a Poison Control Center right away.

DOSAGE AND ADMINISTRATION

Spray on the surface of objects or human skin

Supervise children under 6 years of age when using this product to avoid swallowing.

STORAGE AND HANDLING

Store between 15-30C (59-86F)
Avoid freezing and excessive heat above 40C (104F)

INACTIVE INGREDIENT

water

PACKAGE LABEL

100ml NDC: 74841-001-01

300ml NDC: 74841-001-02

1000ml NDC: 74841-001-03